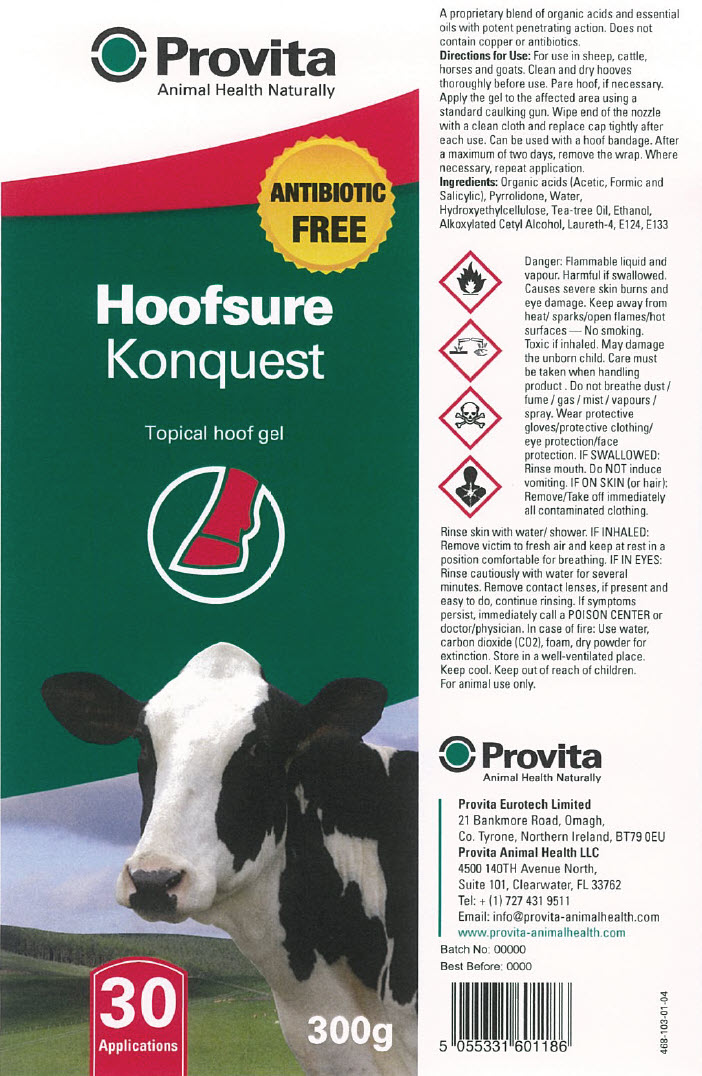 DRUG LABEL: Provita Konquest
NDC: 16371-104 | Form: GEL
Manufacturer: Provita Eurotech Ltd
Category: animal | Type: OTC ANIMAL DRUG LABEL
Date: 20230811

ACTIVE INGREDIENTS: FORMIC ACID 14.5 g/100 g
INACTIVE INGREDIENTS: ALCOHOL; WATER; CETYL ALCOHOL; LAURETH-4; FD&C BLUE NO. 1; PONCEAU 4R; ACETIC ACID; TEA TREE OIL; SALICYLIC ACID; PYRROLIDONE; CARBOXYMETHYLCELLULOSE

Hoofsure Konquest

VETERINARY INDICATIONS

A proprietary blend of organic acids and essential oils with potent penetrating action. Does not contain copper or antibiotics.

Directions for Use

For use in sheep, cattle, horses and goats. Clean and dry hooves thoroughly before use. Pare hoof, if necessary. Apply the gel to the affected area using a standard caulking gun. Wipe end of the nozzle with a clean cloth and replace cap tightly after each use. Can be used with a hoof bandage. After a maximum of two days, remove the wrap. Where necessary, repeat application.

Precautions

Care must be taken when handling product.

Wear suitable protective clothing and eye protection.

Do not breathe vapour.

Contains Formic Acid.

Causes burns.

In case of contact with eyes, rinse immediately with plenty of water and seek medical advice.

Keep out of reach of children.

See Health and Safety Data Sheet.

For external use only.

For animal use only.

Keep Cool.

Ingredients

Organic acids (Acetic, Formic and Salicylic), Pyrrolidone, Water, Hydroxyethylcellulose, Tea-tree Oil, Ethanol, Alkoxylated Cetyl Alcohol, Laureth-4, E124, E133

Provita Eurotech Limited
21 Bankmore Road, Omagh,
Co. Tyrone, Northern Ireland, BT79 0EU

Provita Animal Health LLC
4500 140TH Avenue North,
Suite 101, Clearwater, FL 33762
Tel: + (1) 727 431 9511
Email: info@provita-animalhealth.com
www.provita-animalhealth.com

PRINCIPAL DISPLAY PANEL - 300 g Cartridge Label

Provita
Animal Health Naturally

ANTIBIOTIC
FREE

Hoofsure
Konquest

Topical hoof gel

30
Applications

300g